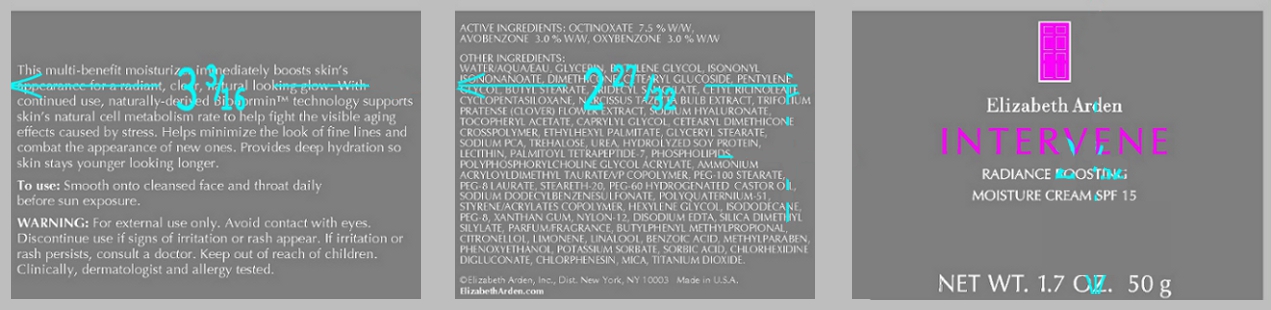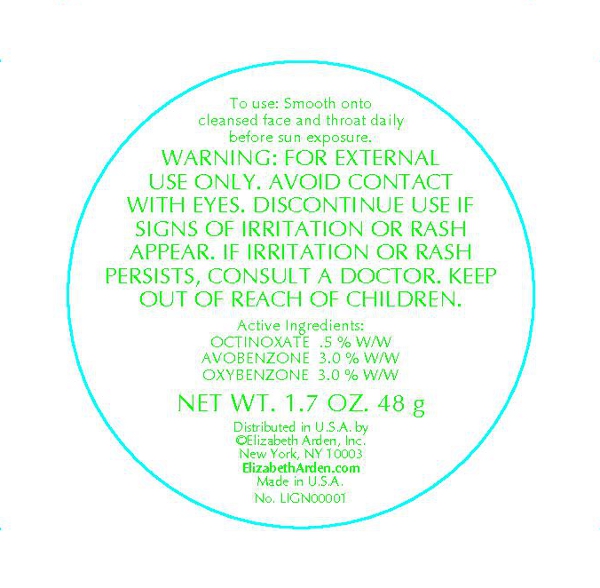 DRUG LABEL: Intervene Radiance Boosting Moisture SPF 15
NDC: 67938-1044 | Form: CREAM
Manufacturer: Elizabeth Arden, Inc
Category: otc | Type: HUMAN OTC DRUG LABEL
Date: 20110113

ACTIVE INGREDIENTS: OCTINOXATE 3.75 g/50 g; AVOBENZONE 1.5 g/50 g; OXYBENZONE 1.5 g/50 g
INACTIVE INGREDIENTS: WATER; GLYCERIN; BUTYLENE GLYCOL; ISONONYL ISONONANOATE; DIMETHICONE; CETEARYL GLUCOSIDE; PENTYLENE GLYCOL; BUTYL STEARATE; CYCLOMETHICONE 5; ETHYLHEXYL PALMITATE; ISODODECANE; GLYCERYL MONOSTEARATE; PEG-100 STEARATE; PHENOXYETHANOL; MICA; POLYETHYLENE GLYCOL 400; SODIUM PYRROLIDONE CARBOXYLATE; UREA; XANTHAN GUM; BENZOIC ACID; POLYOXYL 60 HYDROGENATED CASTOR OIL; NARCISSUS TAZETTA BULB; CHLORPHENESIN; PEG-8 LAURATE; EDETATE DISODIUM; TREHALOSE; STEARETH-20; SORBIC ACID; METHYLPARABEN; CAPRYLYL GLYCOL; SODIUM DODECYLBENZENESULFONATE; TRIFOLIUM PRATENSE FLOWER; HYALURONATE SODIUM; STANNIC OXIDE; ALPHA-TOCOPHEROL; CHLORHEXIDINE GLUCONATE; POTASSIUM SORBATE; HEXYLENE GLYCOL; PROPYLPARABEN; PALMITOYL TETRAPEPTIDE-7

BC1044

DESCRIPTION

This multi-benefit moisturizer immediately boosts skin's appearance for a radiant, clearn, natural looking glow. With continued use, naturally-derived Biodormin technology supports skin's natural cell metabolism rate to help fight the visible aging effects caused by stress. Helps minimize the look of fine lines and combat the appearance of new ones. Provides deep hydration so skin stays younger looking longer. Clinically, dermatologist and allergy tested.

INDICATIONS AND USAGE

To Use: Smooth on to cleansed face and throat daily before sun exposure.

WARNINGS

Warning: For extrenal used only. Avoid contact with eyes. Discontinue use if signs of irritation or rash appear. If irritation or rash persists, consult a doctor. Keep out of reach of children.

OTC - ACTIVE INGREDIENT

Active Ingredients: Octinoxate 7.5% w/w, Avobenzone 3.0% w/w, Oxybenzone 3.0% w/w.

INACTIVE INGREDIENT

Other Ingredients: Water/Aqua/Eau, Ethylhexyl Methoxycinnamate, Glycerin, Butylene Glycol, Isononyl Isononanoate, Dimethicone, Cetearyl Glucoside, Benzophenone-3, Butyl Methoxydibenzoylmethane, Pentylene Glycol, Butyl Stearate, Tidecyl Salicylate, Cetyl Ricinoleate, Cyclopentasiloxane, Narcissus Tazetta Bulb Extract, Triolium Pratense (Clover) Flower Extract, Sodium Hyaluronate, Tocopherold, Tocopheryl Acetate, Caprylyl Glycol, Cetearyl Dimethicone Crosspolymer, Ethylhexyl Palmitate, Glyceryl Stearate, Sodium PCA, Trehalose, Urea, Hydrolyzed Soy Protein, Lecithin, Palmitoyl Tetrapeptide-7, Phospholipids, Polyphosphorylcholine Glycol Acrylate, Ammonium Acryloyldimethyltaurate/VP Copolymer, PEG-100 Stearate, PEG-8 Laurate, Steareth-20, PEG-60 Hydrogenated Castor Oil, Sodium Dodecylbenzenesulfonate, Polyquaternium-51, Styrene/Acrylates Copolymer, Hexylene Glycol, Isododecane, PEG-8, Zanthan Gum, Nylon-12, Disodium EDTA, Mica, Tin Oxide, Silica Dimethyl Silylate, Parfum/Fragrance, Butylphenyl Methylpropional, Citronellol, Limonene, Linalool, Benzoic Acid, Methylparaben, Phenoxyethanol, Postassium Sorbate, Propylparaben, Sorbic Acid, Chlorhexidine Digluconate, Chlorphenesin, Titanium Dioxide (CI 77891).

DOSAGE & ADMINISTRATION

Smooth on to face and throat.

OTC - KEEP OUT OF REACH OF CHILDREN

Keep out of reach of children.

OTC - PURPOSE

Provides SPF 15 sun protection.

OTC - WHEN USING

Avoid contact with eyes.